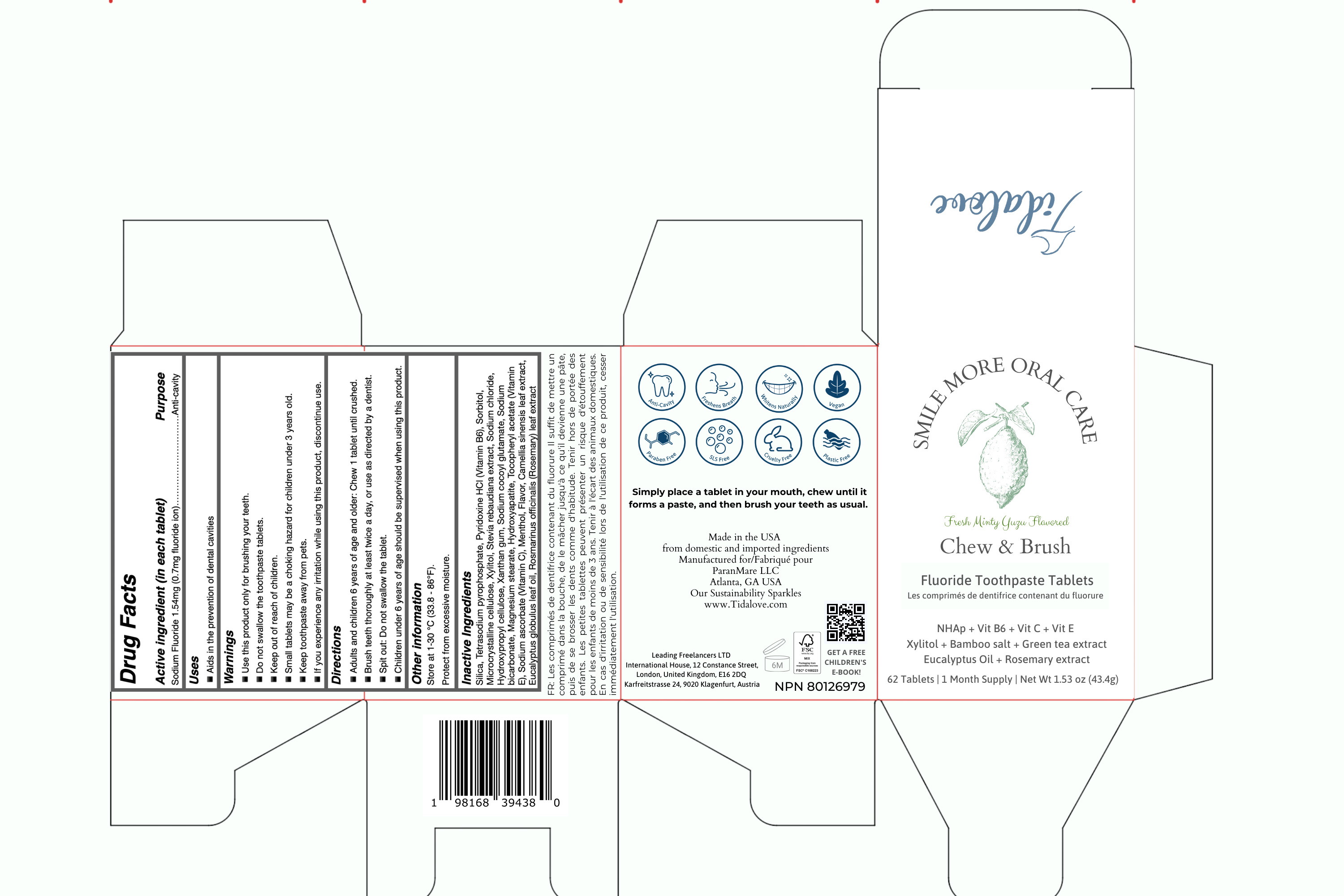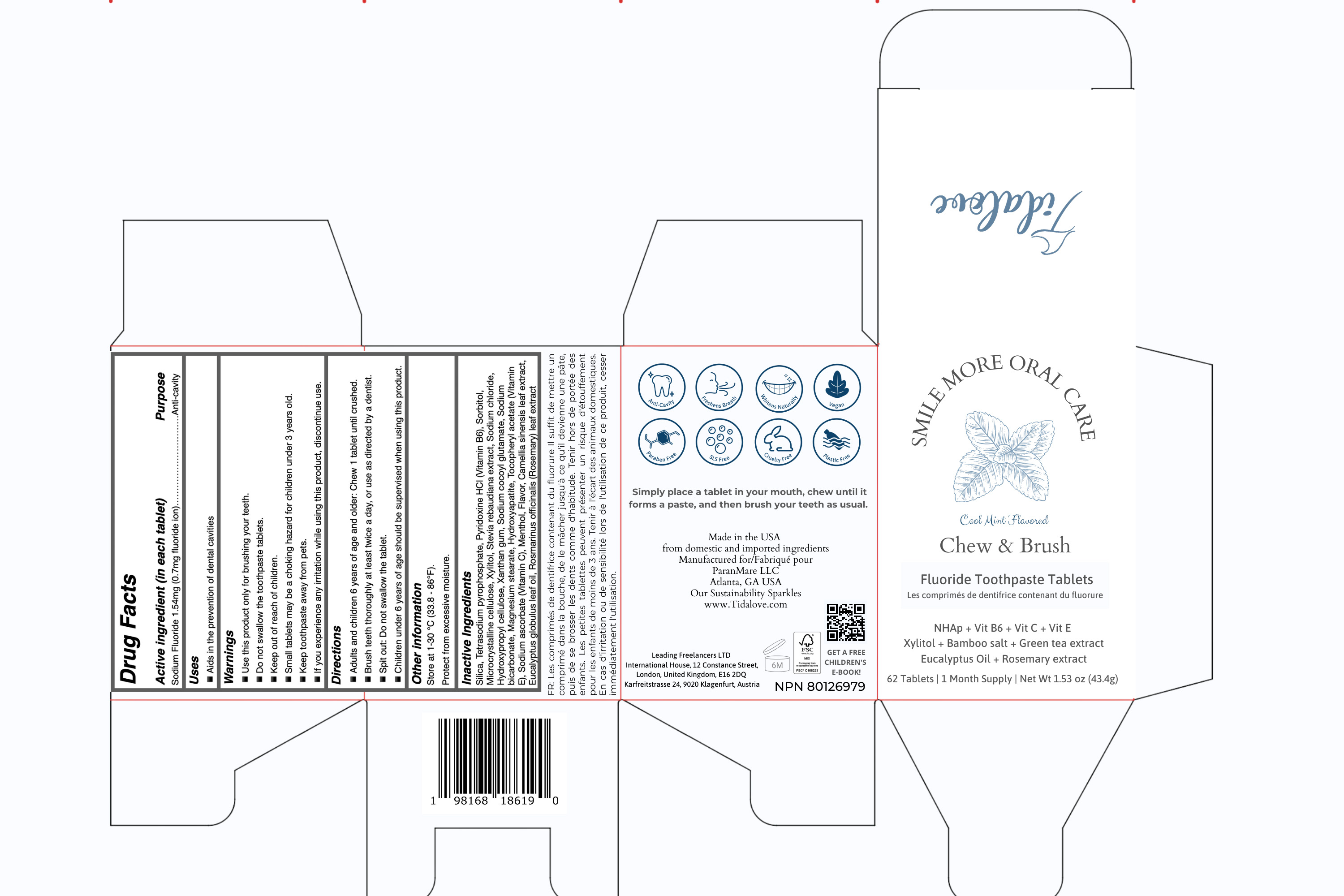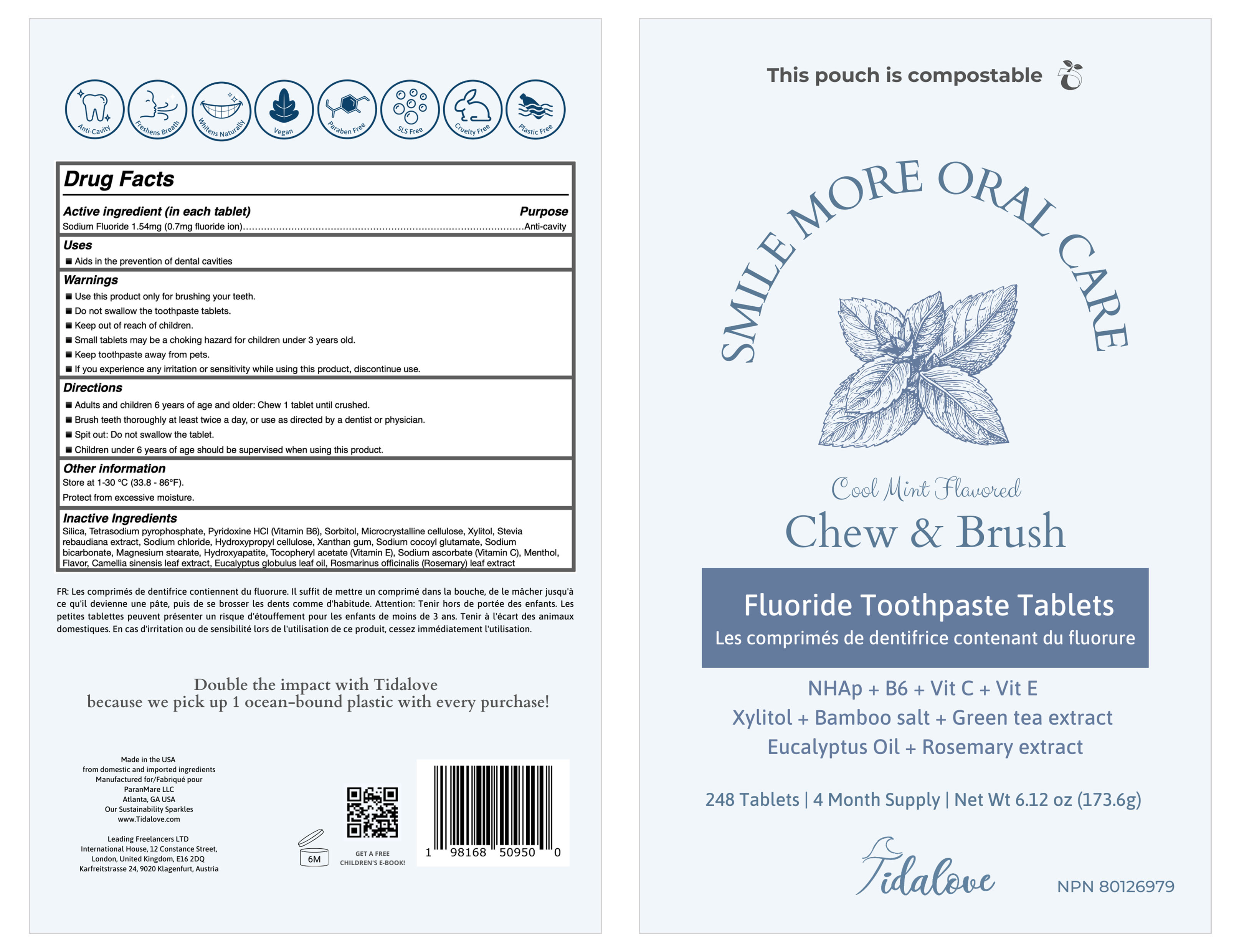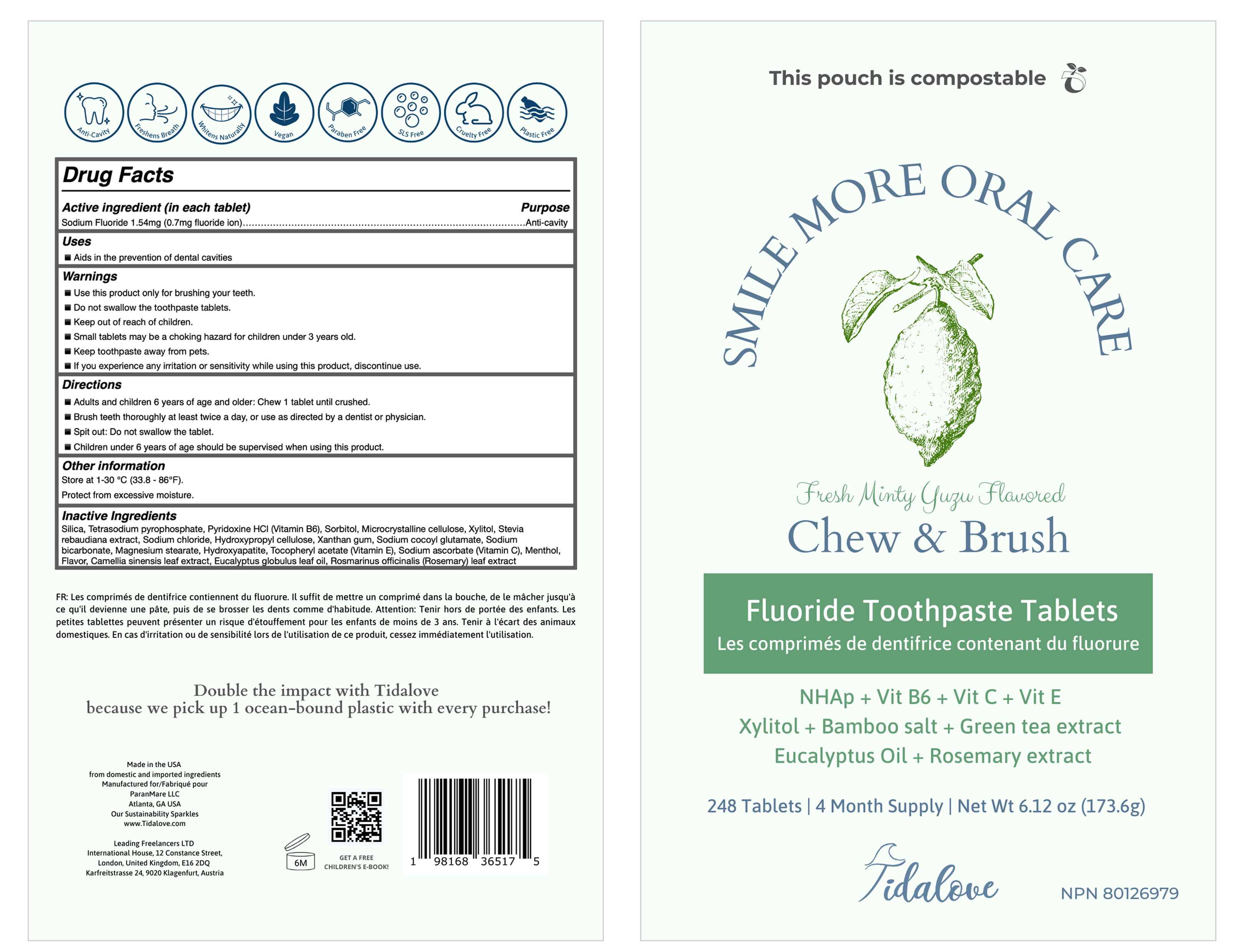 DRUG LABEL: Tooth
NDC: 83861-002 | Form: TABLET
Manufacturer: Henan Dailygreen Biotechnology Co. LTD
Category: otc | Type: HUMAN OTC DRUG LABEL
Date: 20240927

ACTIVE INGREDIENTS: SODIUM FLUORIDE 1.54 mg/100 g
INACTIVE INGREDIENTS: SODIUM PYROPHOSPHATE; PYRIDOXINE; SILICON DIOXIDE; SORBITOL; MAGNESIUM STEARATE; .ALPHA.-TOCOPHEROL ACETATE; EUCALYPTUS OIL; ROSEMARY; XYLITOL; SODIUM COCOYL GLUTAMATE; SODIUM BICARBONATE; TRIBASIC CALCIUM PHOSPHATE; HYDROXYPROPYL CELLULOSE, UNSPECIFIED; STEVIA REBAUDIANA WHOLE; XANTHAN GUM; SODIUM ASCORBATE; GREEN TEA LEAF; MENTHOL; MICROCRYSTALLINE CELLULOSE; SODIUM CHLORIDE

83861-002

Active ingredient

Sodium Fluoride 1.54mg (0.7mg fluoride ion)

Purpose

Anti-cavity

Use

Aids in the prevention of dental cavities

Warnings

- Use this product only for brushing your teeth.

- Do not swallow the toothpaste tablets.

- Keep out of reach of children.

- Small tablets may be a choking hazard for children under 3 years old.

- Keep toothpaste away from pets.

- If you experience any irritation or sensitivity while using this product, discontinue use.

DO NOT USE

N/A

WHEN USING

n/a

STOP USE

If you experience any irritation or sensitivity while using this product, discontinue use.

Keep out of reach of children.

Directions

- Adults and children 6 years of age and older: Chew 1 tablet until crushed.

- Brush teeth thoroughly at least twice a day, or use as directed by a dentist or physician.

- Spit out: Do not swallow the tablet.

- Children under 6 years of age should be supervised when using this product.

Other Information

Store at 1-30 °℃ (33.8 - 86°F).

Protect from excessive moisture.

Inactive ingredients

Silica, Tetrasodium pyrophosphate, Pyridoxine HCI (Vitamin B6), Sorbitol, Microcrystalline cellulose, Xylitol, Stevia rebaudiana extract, Sodium chloride, Hydroxypropyi cellulose, Xanthan gum, Sodium cocoyl glutamate, Sodium bicarbonate, Magnesium stearate, Hydroxyapatite, Tocopheryl acetate (Vitamin E), Sodium ascorbate (Vitamin C), Menthol, Flavor, Camellia sinensis leaf extract, Eucalyptus globulus leaf oil, Rosmarinus officinalis (Rosemary) leaf extract